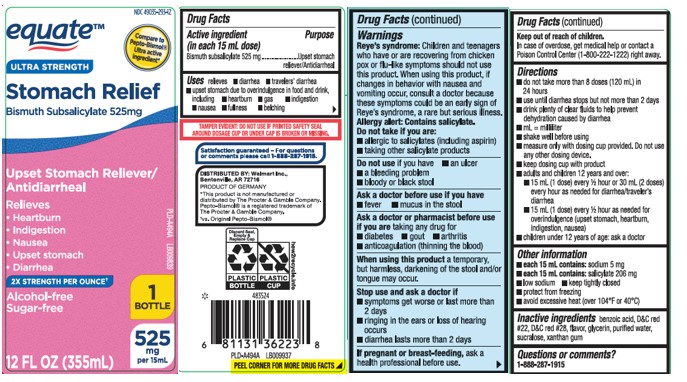 DRUG LABEL: Stomach Relief Ultra
NDC: 49035-293 | Form: LIQUID
Manufacturer: EQUATE (Wal-Mart Stores, Inc.) (see also WAL-MART INC)
Category: otc | Type: HUMAN OTC DRUG LABEL
Date: 20251216

ACTIVE INGREDIENTS: BISMUTH SUBSALICYLATE 525 mg/15 mL
INACTIVE INGREDIENTS: BENZOIC ACID; D&C RED NO. 22; D&C RED NO. 28; GLYCERIN; WATER; SUCRALOSE; XANTHAN GUM

Drug Facts

Active ingredient (in each 15 mL)

Bismuth subsalicylate 525 mg

Purpose

Upset stomach reliever/Antidiarrheal

Uses

relieves

- travelers' diarrhea
- diarrhea
- upset stomach due to overindulgence in food and drink, including:
  - heartburn
  - indigestion
  - nausea
  - gas
  - fullness
  - belching

Warnings

Reye's syndrome: Children and teenagers who have or are recovering from chicken pox or flu-like symptoms ahould not use this product. When using this product, if changes in behavior with nausea and vomiting occur, consult a doctor because these symptoms could be an early sign of Reye's syndrome, a rare but serious illness.

Allergy alert: Contains salicylate. Do not take if you are

- allergic to salicylates (including aspirin)
- taking other salicylate products

Do not use

if you have

- an ulcer
- a bleeding problem
- bloody or black stool

Ask a doctor before use if you have

- fever
- mucus in the stool

Ask a doctor or pharmacist before use if you are

taking any drug for

- diabetes
- gout
- arthritis
- anticoagulation (thinning the blood)

When using this product

a temporary, but harmless, darkening of the stool and/or tongue may occur.

Stop use and ask a doctor if

- symptoms get worse or last more than 2 days
- ringing in the ears or loss of hearing occurs
- diarrhea lasts more than 2 days

If pregnant or breast-feeding,

ask a health professional before use.

Keep out of reach of childen.

In case of overdose, get medical help or contact a Posion Control Center (1-800-222-1222) right away.

Directions

- do not take more than 8 doses (120 mL) in 24 hours
- use until diarrhea stops but not more than 2 days
- drink plenty of clear fluids to help prevent dehydration caused by diarrhea
- mL = milliliter
- shake well before using
- measure only with dosing cup provided. Do not use any other dosing device
- keep dosing cup with product
- adults and children 12 years and over:
  - 15 mL (1dose) every 1/2 or 30 mL (2 doses) every hour as needed diarrhea/traveler's diarrhea
  - 15 mL (1 dose) every 1/2 hour as needed for overindulgence (upset stomach, heartburn, indigestion, nausea)
- children under 12 years of age: ask a doctor

Other information

- each 15 mL contains: sodium 5 mg
- each 15 mL contains: salicylate 206 mg
- low sodium
- keep tightly closed
- protect from freezing
- avoid excessive heat (over 104ºF or 40ºC)

Inactive ingredients

benzoic acid, D&C red #22, D&C red #28, flavor, glycerin, purified water, sucralose, xanthan gum

Questions or comments?

Call 1-8898-287-1915

Principal Display Panel

*Compare to the active ingredient in Pepto-Bismol® Ultra

ULTRA STRENGTH

Stomach Relief

Bismuth Subsalicylate 525 mg

Upset Stomach Reliever/Antidiarrheal

Relieves

- Heartburn
- Indigestion
- Nausea
- Upset Stomach
- Diarrhea

2x Strength Per Ounce†

Alcohol Free

Sugar Free

FL OZ (mL)

†This product is not manufactured or distributed by The Procter & Gamble Company. Pepto-Bismol® is a registered trademark of The Procter & Gamble Company.

TAMPER EVIDENT; DO NOT USE IF PRINTED SAFETY SEAL AROUND DOSAGE CUP OR UNDER CAP IS BROKEN OR MISSING.

DISTRIBUTED BY:

WalMart Inc.,

Bentonville, AR 72716

Package Label

EQUATE Ultra Strength Stomach Relief